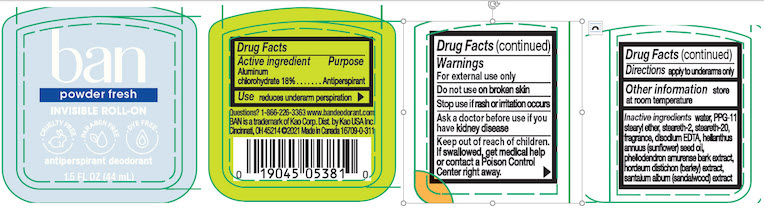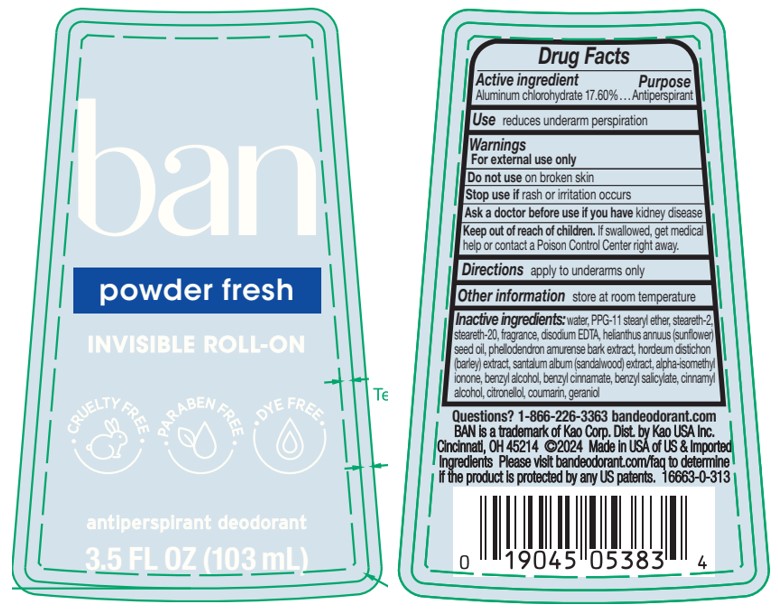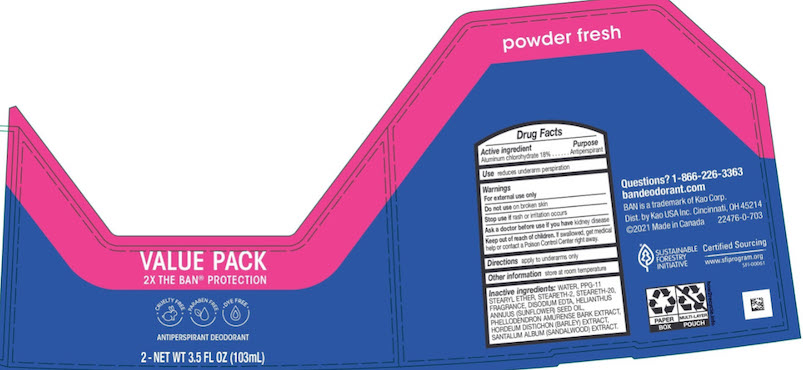 DRUG LABEL: Ban
NDC: 10596-337 | Form: LIQUID
Manufacturer: Kao USA Inc.
Category: otc | Type: HUMAN OTC DRUG LABEL
Date: 20241008

ACTIVE INGREDIENTS: ALUMINUM CHLOROHYDRATE 20 g/103 mL
INACTIVE INGREDIENTS: SUNFLOWER OIL; PPG-11 STEARYL ETHER; WATER; STEARETH-2; STEARETH-20; SANDALWOOD; PHELLODENDRON AMURENSE BARK; BARLEY; EDETATE DISODIUM

Ban Roll-On Antiperspirant Deodorant Powder Fresh

Drug Facts

Active ingredient

Aluminum chlorohydrate 18%

Purpose

Antiperspirant

Use

reduces underarm perspiration

Warnings

For external use only

Do not use on broken skin

Stop use if rash or irritation occurs

Ask a doctor before use if you have kidney disease

Keep out of reach of children. If swallowed, get medical help or contact a Poison Control Center right away.

Directions

apply to underarms only

Other information

store at room temperature

Inactive ingredients

water, PPG-11 stearyl ether, steareth-2, steareth-20, fragrance, disodium EDTA, helianthus annus (sunflower) seed oil, phellodendron amurense bark extract, hordeum distichon (barley) extract, santalum album (sandalwood) extract

Questions? 1-866-226-3363

www.bandeodorant.com

BAN is a trademark of Kao Corp.

Dist. by Kao USA Inc. Cincinnati, OH 45214

©2021 Made in Canada

44 ML PACKAGE

ban

powder fresh
INVISIBLE ROLL-ON

CRUELTY FREE • PARABEN FREE • DYE FREE

1.5 FL OZ (44 mL)

103 mL PACKAGE

ban

powder fresh
INVISIBLE ROLL-ON

CRUELTY FREE • PARABEN FREE • DYE FREE

antiperspirant deodorant

3.5 FL OZ (103 mL)

VALUE PACK

2X THE BAN PROTECTION

CRUELTY FREE • PARABEN FREE • DYE FREE

ANTIPERSPIRANT DEODORANT

2 - NET WT 3.5 FL OZ (103 mL)